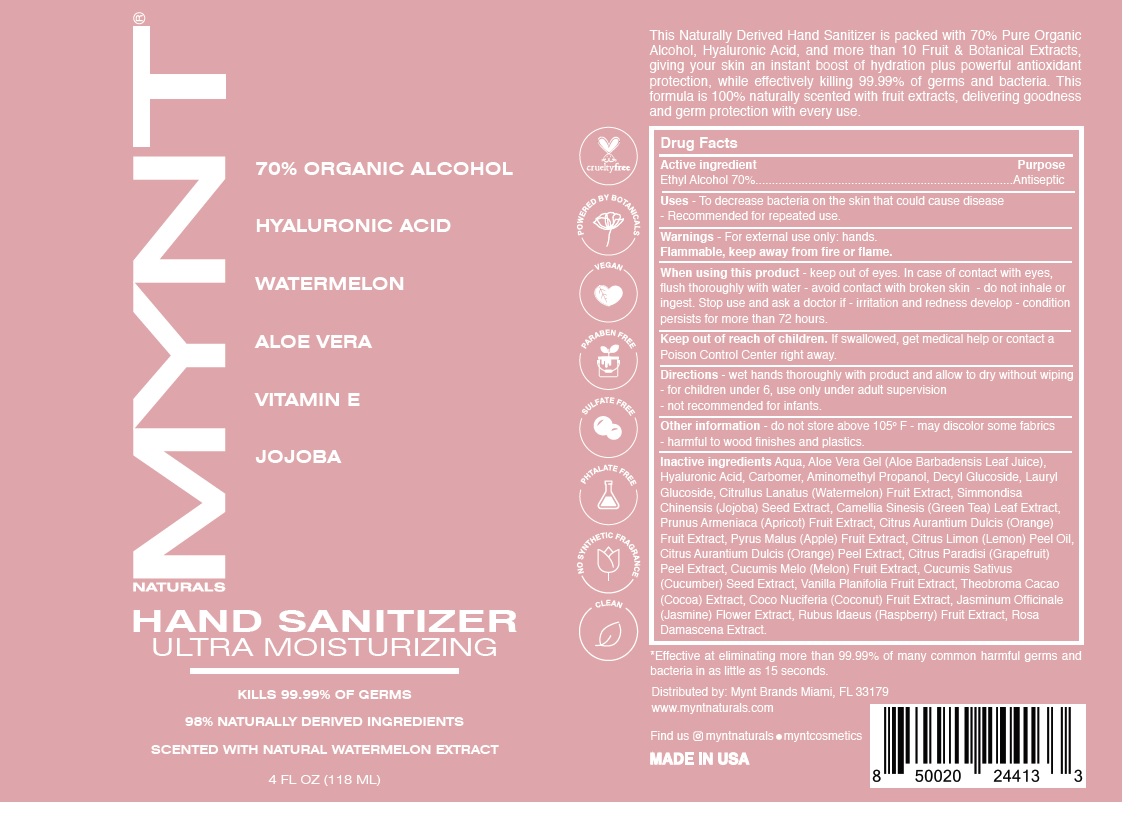 DRUG LABEL: MYNT NATURALS SCENTED HAND SANITIZER WATERMELON
NDC: 79442-104 | Form: GEL
Manufacturer: Prive International Inc.
Category: otc | Type: HUMAN OTC DRUG LABEL
Date: 20201023

ACTIVE INGREDIENTS: ALCOHOL 70 mL/100 mL
INACTIVE INGREDIENTS: WATER; ALOE VERA LEAF; HYALURONIC ACID; CARBOMER HOMOPOLYMER, UNSPECIFIED TYPE; AMINOMETHYLPROPANOL; DECYL GLUCOSIDE; LAURYL GLUCOSIDE; WATERMELON; SIMMONDSIA CHINENSIS SEED; GREEN TEA LEAF; APRICOT; ORANGE; APPLE; LEMON OIL; ORANGE PEEL; GRAPEFRUIT PEEL; MUSKMELON; CUCUMBER SEED; VANILLA BEAN; COCOA; COCONUT; JASMINUM OFFICINALE FLOWER; RASPBERRY; ROSA X DAMASCENA WHOLE

MYNT® NATURALS HAND SANITIZER SCENTED WITH NATURAL WATERMELON EXTRACT

Active ingredient

Ethyl Alcohol 70%

Purpose

Antiseptic

INDICATIONS AND USAGE

Uses - To decrease bacteria on the skin that could cause disease - Recommended for repeated use.

Warnings - For external use only: hands.

Flammable, keep away from fire or flame.

When using this product - keep out of eyes. In case of contact with eyes, flush thoroughly with water - avoid contact with broken skin - do not inhale or ingest. Stop use and ask a doctor if - irritation and redness develop - condition persists for more than 72 hours.

Keep out of reach of children. If swallowed, get medical help or contact a Poison Control Center right away.

DOSAGE AND ADMINISTRATION

Directions - wet hands thoroughly with product and allow to dry without wiping - for children under 6, use only under adult supervision - not recommended for infants.

Other information - do not store above 105° F - may discolor some fabrics - harmful to wood finishes and plastics.

INACTIVE INGREDIENT

Inactive ingredients Aqua, Aloe Vera Gel (Aloe Barbadensis Leaf Juice), Hyaluronic Acid, Carbomer, Aminomethyl Propanol, Decyl Glucoside, Lauryl Glucoside, Citrullus Lanatus (Watermelon) Fruit Extract, Simmondisa Chinensis (Jojoba) Seed Extract, Camellia Sinesis (Green Tea) Leaf Extract, Prunus Armeniaca (Apricot) Fruit Extract, Citrus Aurantium Dulcis (Orange) Fruit Extract, Pyrus Malus (Apple) Fruit Extract, Citrus Limon (Lemon) Peel Oil, Citrus Aurantium Dulcis (Orange) Peel Extract, Citrus Paradisi (Grapefruit) Peel Extract, Cucumis Melo (Melon) Fruit Extract, Cucumis Sativus (Cucumber) Seed Extract, Vanilla Planifolia Fruit Extract, Theobroma Cacao (Cocoa) Extract, Coco Nuciferia (Coconut) Fruit Extract, Jasminum Officinale (Jasmine) Flower Extract, Rubus Idaeus (Raspberry) Fruit Extract, Rosa Damascena Extract.

70% ALCOHOL

HYALURONIC ACID

WATERMELON

ALOE VERA

VITAMIN E

JOJOBA

ULTRA MOISTURIZING

KILLS 99.99% OF GERMS

MADE WITH 98% NATURALLY DERIVED INGREDIENTS

SCENTED WITH NATURAL WATERMELON EXTRACT

cruelty free

POWERED BY BOTANICALS

VEGAN

PARABEN FREE

SULFATE FREE

PHTALATE FREE

NO SYNTHETIC FRAGRANCE

CLEAN

This naturally derived hand sanitizer is packed with 70% Premium Alcohol, Hyaluronic Acid, and more than 10 fruit and botanical extracts, giving your skin an instant boost of hydration plus powerful antioxidant protection, while effectively killing 99.99% of germs and bacteria. This formula is 100% naturally scented with fruit extracts, delivering goodness and germ protection with every use.

*Effective at eliminating more than 99.99% of many common harmful germs and bacteria in as little as 15 seconds.

Distributed by: Mynt Brands Miami, FL 33179

www.myntnaturals.com

Find us myntnaturals • myntcosmetics

MADE IN USA